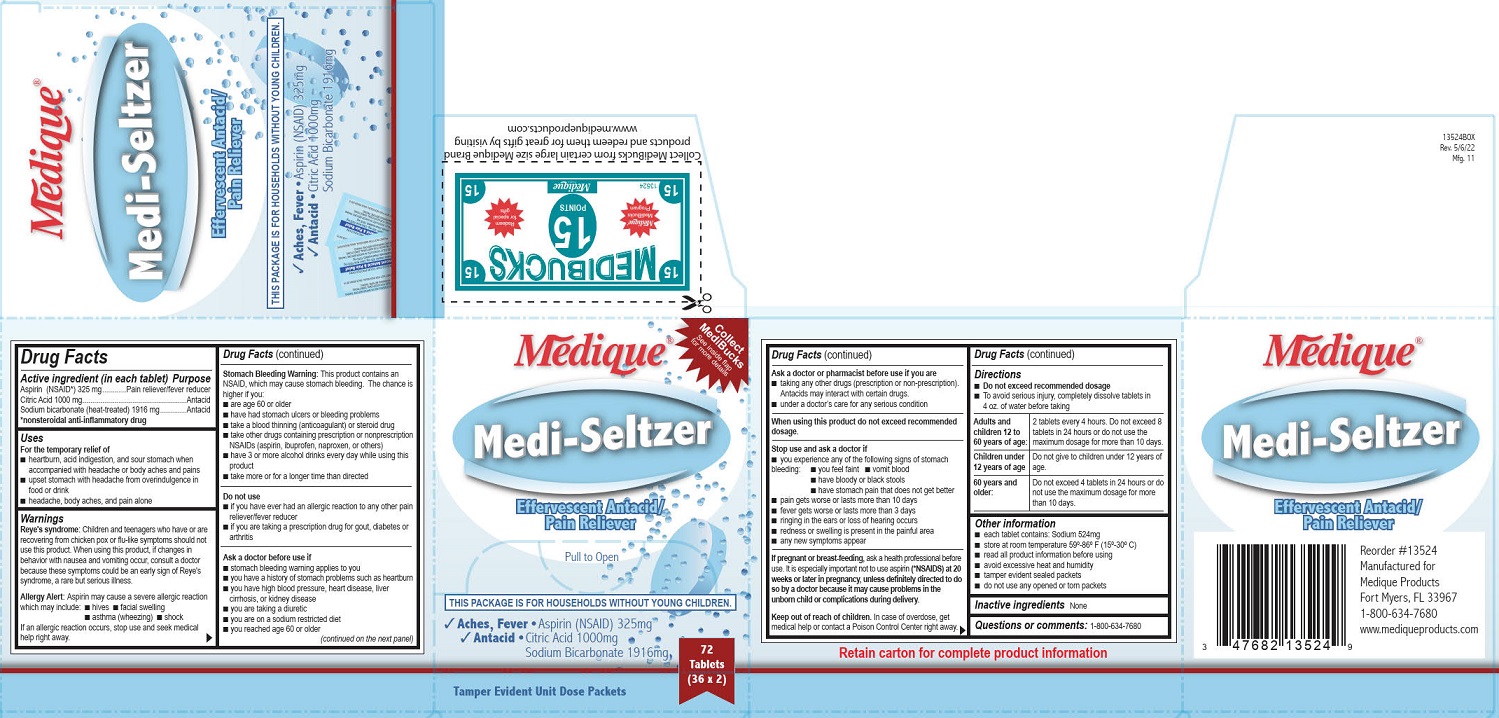 DRUG LABEL: Medique Medi Seltzer
NDC: 47682-135 | Form: TABLET, EFFERVESCENT
Manufacturer: Unifirst First Aid Corporation
Category: otc | Type: HUMAN OTC DRUG LABEL
Date: 20250819

ACTIVE INGREDIENTS: ASPIRIN 325 mg/1 1; CITRIC ACID MONOHYDRATE 1000 mg/1 1; SODIUM BICARBONATE 1916 mg/1 1

Medique Medi Seltzer

Drug Facts

Active ingredient (in each tablet)

Aspirin (NSAID*) 325 mg

Citric Acid 1000 mg

Sodium bicarbonate (heat-treated) 1916 mg

*nonsteriodal anti-inflammatory drug

Purpose

Pain reliever /fever reducer

Antacid

Antacid

Uses

For the temporary relief of

- heartburn, acid indigestion, and sour stomach when accompanied with headache or body aches and pains
- upset stomach with headache from overindulgence in food or drink
- headache, body aches, and pain alone

Warnings

Reye's syndrome: Children and teenagers who have or are recovering from chicken pox or flu-like symptoms should not use this product. When using this product, if changes in behavior with nausea and vomiting occur, consult a doctor because these symptoms could be an early sign of Reye's syndrome, a rare but serious illness.

Allergy alert: Aspirin may cause a severe allergic reaction which may include:

- hives
- facial swelling
- asthma (wheezing)
- shock

If an allergic reaction occurs, stop use and seek medical help right away.

Stomach bleeding warning: This product contains an NSAID, which may cause severe stomach bleeding. The chance is higher if you:

- are age 60 or older
- have had stomach ulcers or bleeding problems
- take a blood thinning (anticoagulant) or steroid drug
- take other drugs containing prescription or nonprescription NSAIDs (aspirin, ibuprofen, naproxen, or others)
- have 3 or more alcohol drinks every day while using this product
- take more or for a longer time than directed

Do not use

- if you have ever had an allergic reaction to any other pain reliever/ fever reducer
- if you are taking a prescription drug for gout, diabetes or arthritis

Ask a doctor before use if

- stomach bleeding warning applies to you
- you have a history of stomach problems such as heartburn
- you have high blood pressure, heart disease, liver cirrhosis, or kidney disease
- you are taking a diuretic
- you are on a sodium restricted diet
- you reached age 60 or older

Ask a doctor or pharmacist before use if you are

- taking any other drugs (prescription or non-prescription). Antacids may interact with certain drugs.
- under a doctor's care for any serious condition

When using this product do not exceed recommended dosage.

Stop use and ask a doctor if

- you experience any of the following signs of stomach bleeding:
  - you feel faint
  - vomit blood
  - have bloody or black stools
  - have stomach pain that does not get better
- pain gets worse or lasts more than 10 days
- fever gets worse or lasts more than 3 days
- you have difficulty swallowing
- ringing in the ears or loss of hearing occurs
- redness or swelling is present in the painful area
- any new symptoms appear

PREGNANCY OR BREAST FEEDING

If pregnant or breast-feeding, ask a health professional before use. It is especially important not to use aspirin (*NSAIDS) at 20 weeks or later in pregnancy unless specifically directed to do so by a doctor because it may cause problems in the unborn child or complications during delivery.

Keep out of reach of children. In case of overdose, get medical help or contact a Poison Control Center right away.

Directions

- do not exceed recommended dosage
- to avoid serious injury, completely dissolve tablets in 4 oz. of water before taking

Adults and children 12 to 60 years of age: 2 tablets every 4 hours. Do not exceed 8 tablets in 24 hours or do not use the maximum dosage for more than 10 days.

Children under 12 years of age: Do not give to children under 12 years of age.

60 years and older: Do not exceed 4 tablets in 24 hours or do not use the maximum dosage for more than 10 days.

Other information

- each tablet contains: Sodium 524 mg
- store at room temperature 59º-86º F (15º-30º C)
- read all product information before using
- avoid excessive heat and humidity
- tamper evident sealed packets
- do not use any opened or torn packets

INACTIVE INGREDIENT

none

Questions or comments? 1-800-634-7680

Medique Medi-Seltzer Label

Medique®

Medi-Seltzer

Effervescent Antacid/Pain Reliever

Pull to Open

This Package is for Households without Young Children.

Aches, Fever ● Aspirin (NSAID) 325 mg

Antacid ● Citric Acid 1000 mg Sodium Bicarbonate 1916 mg

72 Tablets

(36 x 2)

Tamper Evident Unit Dose Packets